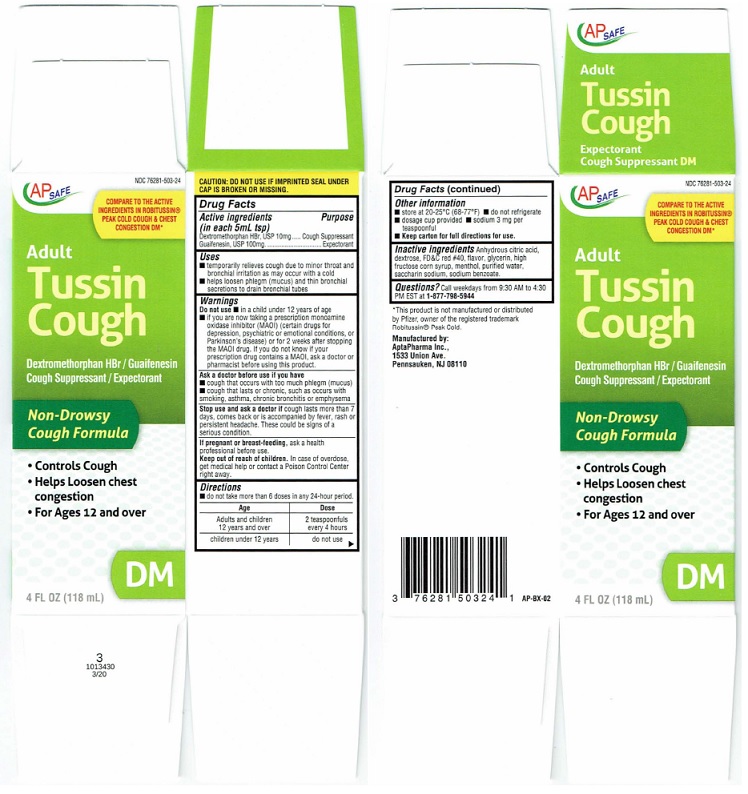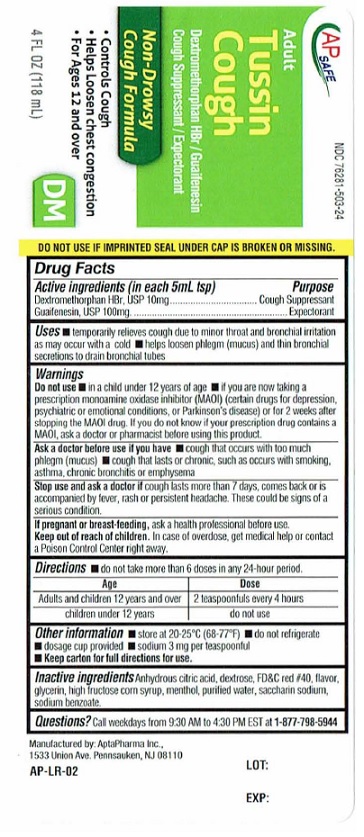 DRUG LABEL: TUSSIN COUGH
NDC: 76281-503 | Form: LIQUID
Manufacturer: AptaPharma Inc.
Category: otc | Type: HUMAN OTC DRUG LABEL
Date: 20231230

ACTIVE INGREDIENTS: DEXTROMETHORPHAN HYDROBROMIDE 10 mg/5 mL; GUAIFENESIN 100 mg/5 mL
INACTIVE INGREDIENTS: ANHYDROUS CITRIC ACID; DEXTROSE; FD&C RED NO. 40; GLYCERIN; HIGH FRUCTOSE CORN SYRUP; MENTHOL; WATER; SACCHARIN SODIUM; SODIUM BENZOATE

Drug Facts

Active ingredients (in each 5mL tsp)
Dextromethorphan HBr, USP 10mg
Guaifenesin, USP 100mg

Purpose
Dextromethorphan HBr, USP .... Cough Suppressant
Guaifenesin, USP .............................. Expectorant

Uses
■ temporarily relieves cough due to minor throat and
bronchial irritation as may occur with acold
■ helps loosen phlegm (mucus) and thin bronchial
secretions to drain bronchial tubes

Warnings
Do not use ■ in a child under 12 years of age
■ if you are now taking aprescription monoamine
oxidase inhibitor (MAOI) (certain drugs for
depression, psychiatric or emotional conditions, or
Parkinson's disease) or for 2 weeks atter stopping
the MAOI drug. If you do not know if your
prescription drug contains a MAOI, ask adoctor or
pharmacist before using this product.

Ask a doctor before use if you have
■ cough that occurs with too much phlegm (mucus)
■ cough that lasts or chronic, such as occurs with
smoking, asthma, chronic bronchitis or emphysema

Stop use and ask a doctor if cough lasts more than 7
days, comes back or is accompanied by fever. rash or
persistent headache. These could be signs of a
serious condition.

If pregnant or breast-feeding, ask ahealth
professional before use.

Keep out of reach of children. In case of overdose,
get medical help or contact a Poison Control Center
right away.

Directions

■ do not take more than 6 doses in any 24-hour period.

------------------------------------------------------------------------

Age Dose
------------------------------------------------------------------------
Adults and children 2 teaspoonfuls
12 years and over every 4 hours
------------------------------------------------------------------------
children under 12 years do not use
_________________________________________

Other information

■ store at 20-25°C (68-77°F) ■ do not refrigerate
■ dosage cup provided ■ sodium 3 mg per
teaspoonful
■ Keep carton for full directions for use.

Inactive ingredientsAnhydrous citric acid,
dextrose, FD&C red #40, flavor, glycerin, high
fructose corn syrup, menthol, purified water.
saccharin sodium, sodium benzoate.

Package Label

AP SAFE NDC 76281-503-24

COMPARE TO THE ACTIVE
INGREDIENTS IN ROBlTUSSIN®
PEAK COLD COUGH & CHEST
CONGESTION DM*

Adult
Tussin
Cough

Dextromethorphan HBr / Guaifenesin

Cough Suppressant / Expectorant

Non-Drowsy
Cough Formula

• Controls Cough
• Helps Loosen chest
congestion
• For Ages 12 and over

DM

4 FL OZ (118 mL)

CAUTION: DO NOT USE IF IMPRINTED SEAL UNDER
CAP IS BROKEN OR MISSING.

3
1013430
3/20

'This product is not manufactured or distributed
by Pfizer, owner of the registered trademark
Robitussin® Peak Cold.

Manufactured by:
AptaPharma Inc.,
1533 Union Ave.
Pennsauken, NJ 08110

AP-BX-02

Carton

Bottle

res